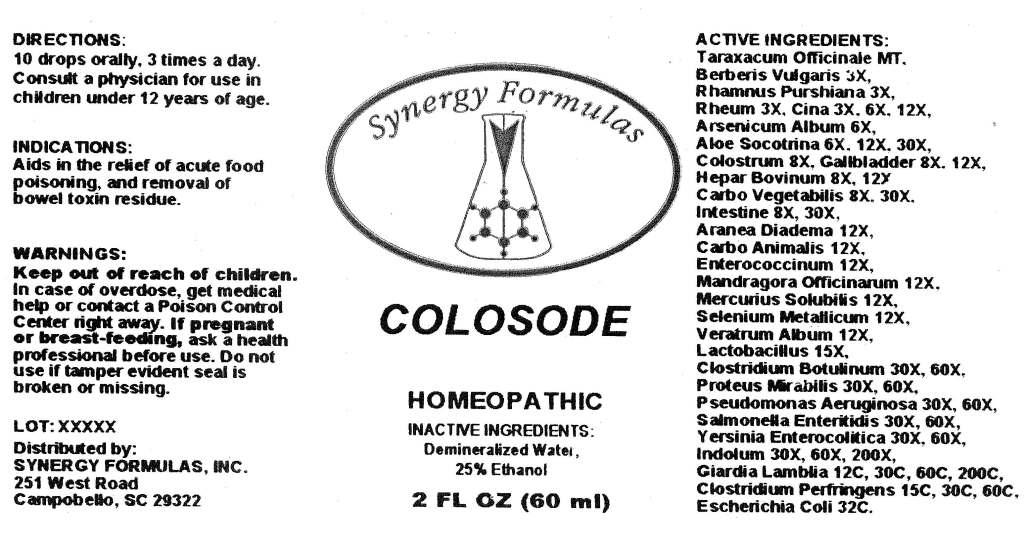 DRUG LABEL: Colosode
NDC: 57520-0349 | Form: LIQUID
Manufacturer: Apotheca Company
Category: homeopathic | Type: HUMAN OTC DRUG LABEL
Date: 20110628

ACTIVE INGREDIENTS: TARAXACUM OFFICINALE 1 [hp_X]/1 mL; BERBERIS VULGARIS ROOT BARK 3 [hp_X]/1 mL; FRANGULA PURSHIANA BARK 3 [hp_X]/1 mL; RHEUM OFFICINALE ROOT 3 [hp_X]/1 mL; ARTEMISIA CINA FLOWER 12 [hp_X]/1 mL; ARSENIC TRIOXIDE 6 [hp_X]/1 mL; ALOE 30 [hp_X]/1 mL; SUS SCROFA GALLBLADDER 12 [hp_X]/1 mL; BEEF LIVER 12 [hp_X]/1 mL; ACTIVATED CHARCOAL 30 [hp_X]/1 mL; PORK INTESTINE 30 [hp_X]/1 mL; ESCHERICHIA COLI 32 [hp_C]/1 mL; ARANEUS DIADEMATUS 12 [hp_X]/1 mL; CARBO ANIMALIS 12 [hp_X]/1 mL; ENTEROCOCCUS FAECALIS 12 [hp_X]/1 mL; MANDRAGORA OFFICINARUM ROOT 12 [hp_X]/1 mL; MERCURIUS SOLUBILIS 12 [hp_X]/1 mL; SELENIUM 12 [hp_X]/1 mL; VERATRUM ALBUM ROOT 12 [hp_X]/1 mL; SALMONELLA ENTERICA SUBSP. ENTERICA SEROVAR ENTERITIDIS 60 [hp_X]/1 mL; PROTEUS MIRABILIS 60 [hp_X]/1 mL; PSEUDOMONAS AERUGINOSA 60 [hp_X]/1 mL; INDOLE 200 [hp_X]/1 mL; CLOSTRIDIUM PERFRINGENS 60 [hp_C]/1 mL; BOTULINUM TOXIN TYPE A 60 [hp_X]/1 mL; GIARDIA LAMBLIA 200 [hp_C]/1 mL; YERSINIA ENTEROCOLITICA 60 [hp_X]/1 mL; COLOSTRUM HUMAN 8 [hp_X]/1 mL; SUS SCROFA GALLBLADDER  12 [hp_X]/1 mL; LACTOBACILLUS ACIDOPHILUS     15 [hp_X]/1 mL
INACTIVE INGREDIENTS: WATER; ALCOHOL

Colosode

ACTIVE INGREDIENT

ACTIVE INGREDIENTS: Taraxacum officinale 1X, Berberis vulgaris 3X, Rhamnus purshiana 3X, Rheum 3X, Cina 3X, 6X, 12X, Arsenicum album 6X, Aloe socotrina 6X, 12X, 30X, Colostrum 8X, Gallbladder 8X, 12X, Hepar bovinum 8X, 12X, Carbo vegetabilis 8X, 30X, Intestine 8X, 30X, Aranea diadema 12X, Carbo animalis 12X, Enterococcinum 12X, Mandragora officinarum 12X, Mercurius solubilis 12X, Selenium metallicum 12X, Veratrum album 12X, Lactobacillus 15X, Clostridium botulinum 30X, 60X, Proteus mirabilis 30X, 60X, Salmonella enteritidis 30X, 60X, Pseudomonas aeruginosa 30X, 60X, Yersinia enterocolitica 30X, 60X, Indolum 30X, 60X, Clostridium perfringens 15C, 30C, 60C, Escherchia coli 32C, Giardia lamblia 12C, 30C, 60C, 200C.

PURPOSE

INDICATIONS: Aids in the relief of acute food poisoning, and removal of bowel toxin residue.

WARNINGS

WARNINGS: Keep out of reach of children. In case of overdose, get medical help or contact a Poison Control Center right away.

If pregnant or breast-feeding, ask a health professional before use.

Do not use if tamper evident seal is broken or missing.

DOSAGE AND ADMINISTRATION

DIRECTIONS: 10 drops orally, 3 times a day. Consult a physician for use in children under 12 years of age.

INACTIVE INGREDIENTS: Demineralized water, 25% Ethanol.

KEEP OUT OF REACH OF CHILDREN. In case of overdose, get medical help or contact a Poison Control Center right away.

INDICATIONS AND USAGE

INDICATIONS: Aids in the relief of acute food poisoning, and removal of bowel toxin residue.

QUESTIONS

Distributed by

SYNERGY FORMULAS, INC.

251 West Road

Campobello, South Carolina

PACKAGE LABEL

Synergy Formulas

COLOSODE

HOMEOPATHIC

2 FL OZ (60 ml)